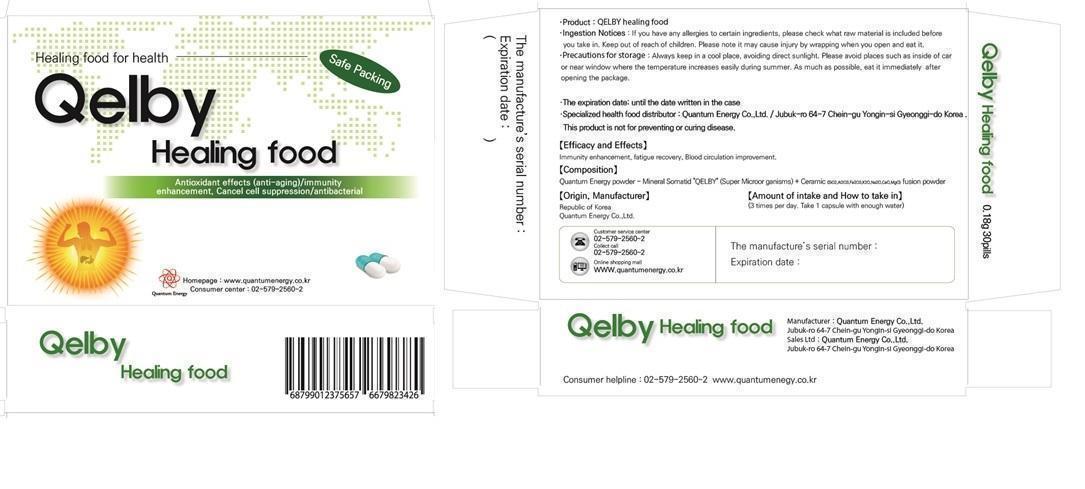 DRUG LABEL: Qelby Healing Food
NDC: 69398-101 | Form: CAPSULE
Manufacturer: Quantum Energy Co., Ltd.
Category: otc | Type: HUMAN OTC DRUG LABEL
Date: 20180220

ACTIVE INGREDIENTS: ASIAN GINSENG 0.05 g/1 1
INACTIVE INGREDIENTS: SILICON DIOXIDE; ALUMINUM OXIDE; POTASSIUM OXIDE; SODIUM OXIDE; LIME (CALCIUM OXIDE)

Qelby Healing Food

ACTIVE INGREDIENT

Red Ginseng 0.05g

PURPOSE

Qelby healing food for health.

Keep out of reach of children

[Efficacy and Effects]

Immunity enhancement, fatigue recovery, Blood circulation improvement

Ingestion Notices:

If you have any allergies to certain ingredients, please check what raw material is included before you take in.

[Amount of intake and How to take in]

3 times per day. Take 1 capsule with enough water

[Composition]

Quantum Energy powder – Mineral Somatid “QELBY” (Super Micro organisms) + Ceramic (SiO2,Ai2O3,Fe2O3,K2O,Na2O, CaO,MgO) fusion powder

Precautions for storage:

Always keep in a cool place, avoiding direct sunlight. Please avoid places such as inside of car or near window where the temperature increases easily during summer. As much as possible, eat it immediately after opening the package. Please note it may cause injury by wrapping when you open and eat it.

Customer service center

82-2-579-2560

Collect call
82-2-579-2560